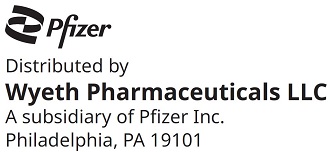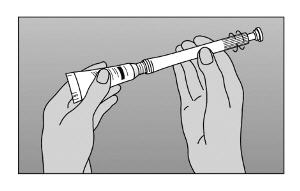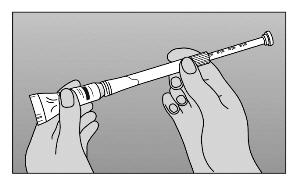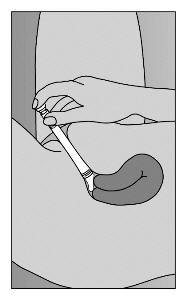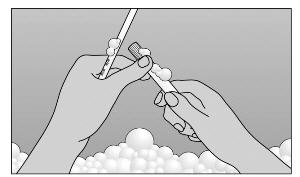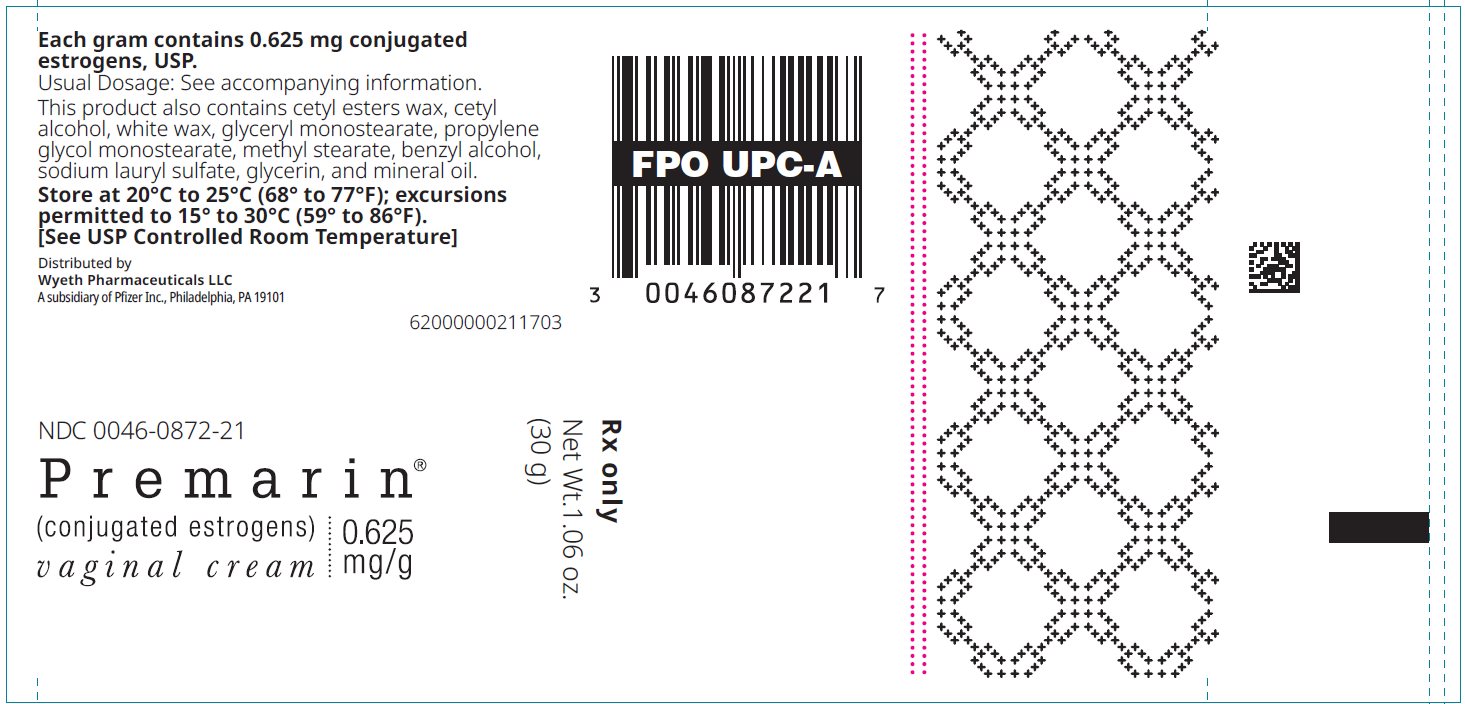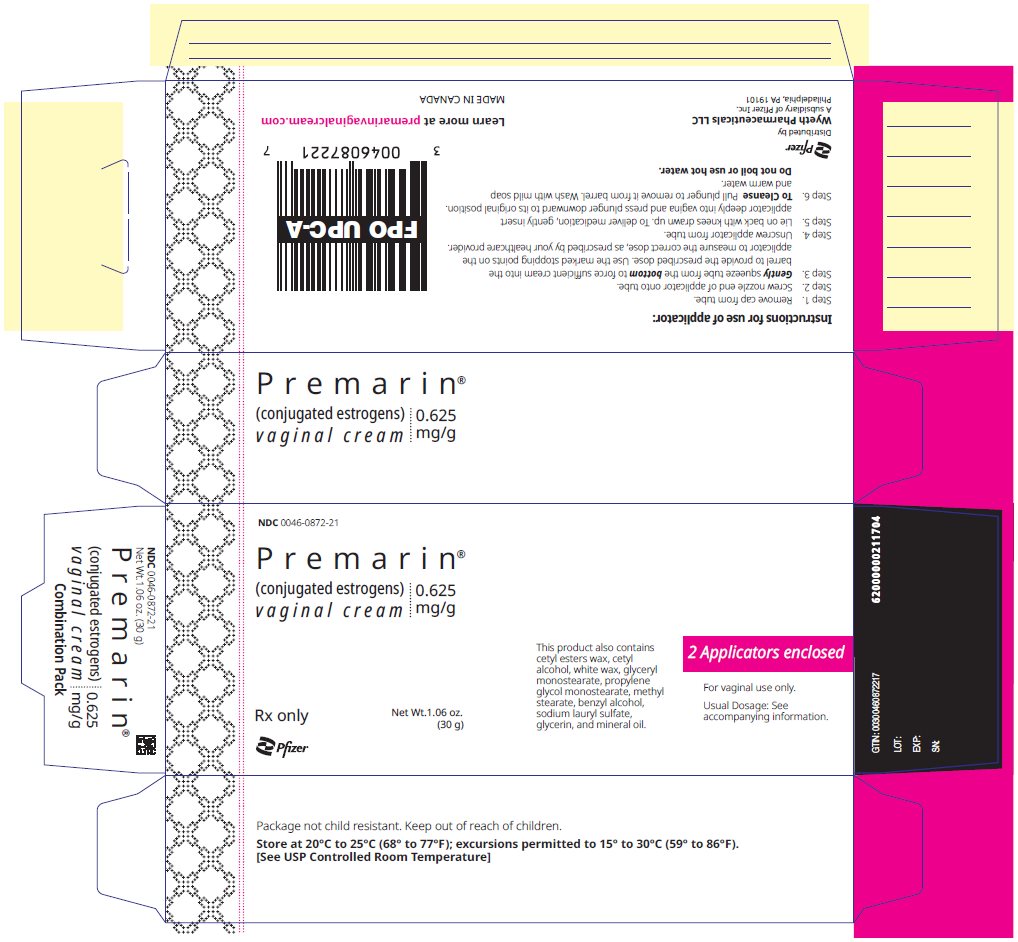 DRUG LABEL: Premarin
NDC: 0046-0872 | Form: CREAM
Manufacturer: Wyeth Pharmaceuticals LLC, a subsidiary of Pfizer Inc.
Category: prescription | Type: HUMAN PRESCRIPTION DRUG LABEL
Date: 20250530

ACTIVE INGREDIENTS: ESTROGENS, CONJUGATED 0.625 mg/1 g
INACTIVE INGREDIENTS: CETYL ALCOHOL; WHITE WAX; GLYCERYL MONOSTEARATE; PROPYLENE GLYCOL MONOPALMITOSTEARATE; METHYL STEARATE; BENZYL ALCOHOL; SODIUM LAURYL SULFATE; GLYCERIN; MINERAL OIL

HIGHLIGHTS OF PRESCRIBING INFORMATION

These highlights do not include all the information needed to use PREMARIN® VAGINAL CREAM safely and effectively. See full prescribing information for PREMARIN VAGINAL CREAM.
PREMARIN (conjugated estrogens) vaginal cream.
Initial U.S. Approval: 1942

WARNING: ENDOMETRIAL CANCER, CARDIOVASCULAR DISORDERS, BREAST CANCER and PROBABLE DEMENTIA

See full prescribing information for complete boxed warning.

Estrogen-Alone Therapy

- There is an increased risk of endometrial cancer in a woman with a uterus who uses unopposed estrogens (5.3)
- Estrogen-alone therapy should not be used for the prevention of cardiovascular disease or dementia (5.2, 5.4)
- The Women's Health Initiative (WHI) estrogen-alone substudy reported increased risks of stroke and deep vein thrombosis (DVT) (5.2)
- The WHI Memory Study (WHIMS) estrogen-alone ancillary study of WHI reported an increased risk of probable dementia in postmenopausal women 65 years of age and older (5.4)

Estrogen Plus Progestin Therapy

- Estrogen plus progestin therapy should not be used for the prevention of cardiovascular disease or dementia (5.2, 5.4)
- The WHI estrogen plus progestin substudy reported increased risks of stroke, DVT, pulmonary embolism (PE), and myocardial infarction (MI) (5.2)
- The WHI estrogen plus progestin substudy reported increased risks of invasive breast cancer (5.3)
- The WHIMS estrogen plus progestin ancillary study of WHI reported an increased risk of probable dementia in postmenopausal women 65 years of age and older (5.4)

1 INDICATIONS AND USAGE

PREMARIN (conjugated estrogens) vaginal cream is a mixture of estrogens indicated for:

- Treatment of Atrophic Vaginitis and Kraurosis Vulvae (1.1)
- Treatment of Moderate to Severe Dyspareunia, a Symptom of Vulvar and Vaginal Atrophy, due to Menopause (1.2)

2 DOSAGE AND ADMINISTRATION

- Cyclic administration of 0.5 to 2 g intravaginally [daily for 21 days then off for 7 days] for Treatment of Atrophic Vaginitis and Kraurosis Vulvae (2.1)
- Cyclic administration of 0.5 g intravaginally [daily for 21 days then off for 7 days] for Treatment of Moderate to Severe Dyspareunia, a Symptom of Vulvar and Vaginal Atrophy, due to Menopause (2.2)
- Twice-weekly administration of 0.5 g intravaginally [for example, Monday and Thursday] for Treatment of Moderate to Severe Dyspareunia, a Symptom of Vulvar and Vaginal Atrophy, due to Menopause (2.2)

3 DOSAGE FORMS AND STRENGTHS

- Each gram contains 0.625 mg conjugated estrogens (3)
- Combination package: Each contains a net wt. 1.06 oz (30 g) tube with plastic applicator(s) calibrated in 0.5 g increments to a maximum of 2 g (3)

4 CONTRAINDICATIONS

- Undiagnosed abnormal genital bleeding (4, 5.3)
- Breast cancer or a history of breast cancer (4, 5.3)
- Estrogen-dependent neoplasia (4, 5.3)
- Active DVT, PE, or a history of these conditions (4, 5.2)
- Active arterial thromboembolic disease (for example, stroke and MI), or a history of these conditions (4, 5.2)
- Known anaphylactic reaction or angioedema to PREMARIN vaginal cream (4, 5.16, 5.17)
- Hepatic impairment or disease (4, 5.11)
- Protein C, protein S, or antithrombin deficiency or other known thrombophilic disorders (4)

5 WARNINGS AND PRECAUTIONS

- Estrogens increase the risk of gallbladder disease (5.5)
- Discontinue estrogen if severe hypercalcemia, loss of vision, severe hypertriglyceridemia or cholestatic jaundice occurs (5.6, 5.7, 5.10, 5.11)
- Monitor thyroid function in women on thyroid replacement therapy (5.12, 5.21)

6 ADVERSE REACTIONS

In a prospective, randomized, placebo-controlled, double-blind study, the most common adverse reactions ≥ 2% are headache, pelvic pain, vasodilation, breast pain, leucorrhea, metrorrhagia, vaginitis, vulvovaginal disorder (6.1)

To report SUSPECTED ADVERSE REACTIONS, contact Pfizer Inc. at 1-800-438-1985 or FDA at 1-800-FDA-1088 or www.fda.gov/medwatch.

7 DRUG INTERACTIONS

Inducers and/or inhibitors of CYP3A4 may affect estrogen drug metabolism (7.1)

8 USE IN SPECIFIC POPULATIONS

- Lactation: Estrogen administration to lactating women has been shown to decrease the quantity and quality of breast milk (8.2)
- Geriatric Use: An increased risk of probable dementia in women over 65 years of age was reported in the Women's Health Initiative Memory ancillary studies of the Women's Health Initiative (5.4, 8.5)

FULL PRESCRIBING INFORMATION

WARNING: ENDOMETRIAL CANCER, CARDIOVASCULAR DISORDERS, BREAST CANCER and PROBABLE DEMENTIA

Estrogen-Alone Therapy

Endometrial Cancer

There is an increased risk of endometrial cancer in a woman with a uterus who uses unopposed estrogens. Adding a progestin to estrogen therapy has been shown to reduce the risk of endometrial hyperplasia, which may be a precursor to endometrial cancer. Adequate diagnostic measures, including directed or random endometrial sampling when indicated, should be undertaken to rule out malignancy in postmenopausal women with undiagnosed persistent or recurring abnormal genital bleeding [see Warnings and Precautions (5.3)].

Cardiovascular Disorders and Probable Dementia

Estrogen-alone therapy should not be used for the prevention of cardiovascular disease or dementia [see Warnings and Precautions (5.2, 5.4), and Clinical Studies (14.2, 14.3)].

The Women's Health Initiative (WHI) estrogen-alone substudy reported increased risks of stroke and deep vein thrombosis (DVT) in postmenopausal women (50 to 79 years of age) during 7.1 years of treatment with daily oral conjugated estrogens (CE) (0.625 mg)-alone, relative to placebo [see Warnings and Precautions (5.2), and Clinical Studies (14.2)].

The WHI Memory Study (WHIMS) estrogen-alone ancillary study of WHI reported an increased risk of developing probable dementia in postmenopausal women 65 years of age or older during 5.2 years of treatment with daily CE (0.625 mg)-alone, relative to placebo. It is unknown whether this finding applies to younger postmenopausal women [see Warnings and Precautions (5.4), Use in Specific Populations (8.5), and Clinical Studies (14.3)].

In the absence of comparable data, these risks should be assumed to be similar for other doses of CE and other dosage forms of estrogens.

Estrogens with or without progestins should be prescribed at the lowest effective doses and for the shortest duration consistent with treatment goals and risks for the individual woman.

Estrogen Plus Progestin Therapy

Cardiovascular Disorders and Probable Dementia

Estrogen plus progestin therapy should not be used for the prevention of cardiovascular disease or dementia [see Warnings and Precautions (5.2, 5.4), and Clinical Studies (14.2, 14.3)].

The WHI estrogen plus progestin substudy reported increased risks of DVT, pulmonary embolism (PE), stroke and myocardial infarction (MI) in postmenopausal women (50 to 79 years of age) during 5.6 years of treatment with daily oral CE (0.625 mg) combined with medroxyprogesterone acetate (MPA) (2.5 mg), relative to placebo [see Warnings and Precautions (5.2), and Clinical Studies (14.2)].

The WHIMS estrogen plus progestin ancillary study of the WHI reported an increased risk of developing probable dementia in postmenopausal women 65 years of age or older during 4 years of treatment with daily CE (0.625 mg) combined with MPA (2.5 mg), relative to placebo. It is unknown whether this finding applies to younger postmenopausal women [see Warnings and Precautions (5.4), Use in Specific Populations (8.5), and Clinical Studies (14.3)].

Breast Cancer

The WHI estrogen plus progestin substudy also demonstrated an increased risk of invasive breast cancer [see Warnings and Precautions (5.3), and Clinical Studies (14.2)].

In the absence of comparable data, these risks should be assumed to be similar for other doses of CE and MPA, and other combinations and dosage forms of estrogens and progestins.

Estrogens with or without progestins should be prescribed at the lowest effective doses and for the shortest duration consistent with treatment goals and risks for the individual woman.

2 DOSAGE AND ADMINISTRATION

Generally, when estrogen is prescribed for a postmenopausal woman with a uterus, a progestin should also be considered to reduce the risk of endometrial cancer [see Boxed Warning].

A woman without a uterus does not need a progestin. In some cases, however, hysterectomized women with a history of endometriosis may need a progestin [see Warnings and Precautions (5.3, 5.15)].

Use of estrogen-alone, or in combination with a progestin, should be with the lowest effective dose and for the shortest duration consistent with treatment goals and risks for the individual woman. Postmenopausal women should be re-evaluated periodically as clinically appropriate to determine if treatment is still necessary.

2.1 Treatment of Atrophic Vaginitis and Kraurosis Vulvae

PREMARIN vaginal cream is administered intravaginally in a cyclic regimen (daily for 21 days and then off for 7 days). Generally, women should be started at the 0.5 g dosage strength. Dosage adjustments (0.5 to 2 g) may be made based on individual response [see Dosage Forms and Strengths (3)].

2.2 Treatment of Moderate to Severe Dyspareunia, a Symptom of Vulvar and Vaginal Atrophy, due to Menopause

PREMARIN vaginal cream (0.5 g) is administered intravaginally in a twice-weekly (for example, Monday and Thursday) continuous regimen or in a cyclic regimen of 21 days of therapy followed by 7 days off of therapy [see Dosage Forms and Strengths (3)].

3 DOSAGE FORMS AND STRENGTHS

Each gram contains 0.625 mg conjugated estrogens, USP.

Combination package: Each contains a net wt. 1.06 oz (30 g) tube with plastic applicator(s) calibrated in 0.5 g increments to a maximum of 2 g.

4 CONTRAINDICATIONS

PREMARIN vaginal cream is contraindicated in women with any of the following conditions:

- Undiagnosed abnormal genital bleeding [see Warnings and Precautions (5.3)]
- Breast cancer or a history of breast cancer [see Warnings and Precautions (5.3)]
- Estrogen-dependent neoplasia [see Warnings and Precautions (5.3)]
- Active DVT, PE, or a history of these conditions [see Warnings and Precautions (5.2)]
- Active arterial thromboembolic disease (for example, stroke and MI), or a history of these conditions [see Warnings and Precautions (5.2)]
- Known anaphylactic reaction or angioedema to PREMARIN [see Warnings and Precautions (5.16,5.17)]
- Hepatic impairment or disease [see Warnings and Precautions (5.11)]
- Protein C, protein S or antithrombin deficiency or other known thrombophilic disorders

5 WARNINGS AND PRECAUTIONS

5.1 Risks from Systemic Absorption

Systemic absorption occurs with the use of PREMARIN vaginal cream. The warnings, precautions, and adverse reactions associated with oral PREMARIN treatment should be taken into account.

5.2 Cardiovascular Disorders

An increased risk of stroke and DVT has been reported with estrogen-alone therapy. An increased risk of PE, DVT, stroke and MI has been reported with estrogen plus progestin therapy. Should any of these events occur or be suspected, estrogen with or without progestin therapy should be discontinued immediately.

Risk factors for arterial vascular disease (for example, hypertension, diabetes mellitus, tobacco use, hypercholesterolemia, and obesity) and/or venous thromboembolism (VTE) (for example, personal history or family history of VTE, obesity, and systemic lupus erythematosus) should be managed appropriately.

Stroke

In the WHI estrogen-alone substudy, a statistically significant increased risk of stroke was reported in women 50 to 79 years of age receiving daily CE (0.625 mg) -alone compared to women in the same age group receiving placebo (45 versus 33 per 10,000 women-years). The increase in risk was demonstrated in Year 1 and persisted [see Clinical Studies (14.2)]. Should a stroke occur or be suspected, estrogen-alone therapy should be discontinued immediately.

Subgroup analyses of women 50 to 59 years of age suggest no increased risk of stroke for those women receiving CE (0.625 mg) -alone versus those receiving placebo (18 versus 21 per 10,000 women-years).^1

In the WHI estrogen plus progestin substudy, a statistically significant increased risk of stroke was reported in women 50 to 79 years of age receiving daily CE (0.625 mg) plus MPA (2.5 mg) compared to women in the same age group receiving placebo (33 versus 25 per 10,000 women-years) [see Clinical Studies (14.2)]. The increase in risk was demonstrated after the first year and persisted.^1 Should a stroke occur or be suspected, estrogen plus progestin therapy should be discontinued immediately.

Coronary Heart Disease

In the WHI estrogen-alone substudy, no overall effect on coronary heart disease (CHD) events (defined as nonfatal MI, silent MI, or CHD death) was reported in women receiving estrogen-alone compared to placebo^2 [see Clinical Studies (14.2)].

Subgroup analyses of women 50 to 59 years of age suggest a statistically non-significant reduction in CHD events (CE [0.625 mg]-alone compared to placebo) in women with less than 10 years since menopause (8 versus 16 per 10,000 women-years).^1

In the WHI estrogen plus progestin substudy, there was a statistically non-significant increased risk of CHD events reported in women receiving daily CE (0.625 mg) plus MPA (2.5 mg) compared to women receiving placebo (41 versus 34 per 10,000 women-years).^1 An increase in relative risk was demonstrated in Year 1, and a trend toward decreasing relative risk was reported in years 2 through 5 [see Clinical Studies (14.2)].

In postmenopausal women with documented heart disease (n = 2,763, average 66.7 years of age), in a controlled clinical trial of secondary prevention of cardiovascular disease (Heart and Estrogen/Progestin Replacement Study; HERS), treatment with daily CE (0.625 mg) plus MPA (2.5 mg) demonstrated no cardiovascular benefit. During an average follow-up of 4.1 years, treatment with CE plus MPA did not reduce the overall rate of CHD events in postmenopausal women with established CHD. There were more CHD events in the CE plus MPA-treated group than in the placebo group in Year 1, but not during the subsequent years. Two thousand, three hundred and twenty-one (2,321) women from the original HERS trial agreed to participate in an open label extension of HERS, HERS II. Average follow-up in HERS II was an additional 2.7 years, for a total of 6.8 years overall. Rates of CHD events were comparable among women in the CE (0.625 mg) plus MPA (2.5 mg) group and the placebo group in HERS, HERS II, and overall.

Venous Thromboembolism (VTE)

In the WHI estrogen-alone substudy, the risk of VTE (DVT and PE) was increased for women receiving daily CE (0.625 mg) -alone compared to placebo (30 versus 22 per 10,000 women-years), although only the increased risk of DVT reached statistical significance (23 versus 15 per 10,000 women-years). The increase in VTE risk was demonstrated during the first 2 years^3 [see Clinical Studies (14.2)]. Should a VTE occur or be suspected, estrogen-alone therapy should be discontinued immediately.

In the WHI estrogen plus progestin substudy, a statistically significant 2-fold greater rate of VTE was reported in women receiving daily CE (0.625 mg) plus MPA (2.5 mg) compared to women receiving placebo (35 versus 17 per 10,000 women-years). Statistically significant increases in risk for both DVT (26 versus 13 per 10,000 women-years) and PE (18 versus 8 per 10,000 women-years) were also demonstrated. The increase in VTE risk was observed during the first year and persisted^4 [see Clinical Studies (14.2)]. Should a VTE occur or be suspected, estrogen plus progestin therapy should be discontinued immediately.

If feasible, estrogens should be discontinued at least 4 to 6 weeks before surgery of the type associated with an increased risk of thromboembolism, or during periods of prolonged immobilization.

5.3 Malignant Neoplasms

Endometrial Cancer

An increased risk of endometrial cancer has been reported with the use of unopposed estrogen therapy in a woman with a uterus. The reported endometrial cancer risk among unopposed estrogen users is about 2 to 12 times greater than in non-users, and appears dependent on duration of treatment and on estrogen dose. Most studies show no significant increased risk associated with use of estrogens for less than 1 year. The greatest risk appears to be associated with prolonged use, with increased risks of 15- to 24-fold for 5 to 10 years or more, and this risk has been shown to persist for at least 8 to 15 years after estrogen therapy is discontinued.

Clinical surveillance of all women using estrogen-alone or estrogen plus progestin therapy is important. Adequate diagnostic measures, including directed or random endometrial sampling when indicated, should be undertaken to rule out malignancy in postmenopausal women with undiagnosed persistent or recurring abnormal genital bleeding.

There is no evidence that the use of natural estrogens results in a different endometrial risk profile than synthetic estrogens of equivalent estrogen dose. Adding a progestin to postmenopausal estrogen therapy has been shown to reduce the risk of endometrial hyperplasia, which may be a precursor to endometrial cancer.

In a 52-week clinical trial using PREMARIN vaginal cream alone (0.5 g inserted twice weekly or daily for 21 days, then off for 7 days), there was no evidence of endometrial hyperplasia or endometrial carcinoma.

Breast Cancer

The WHI substudy of daily CE (0.625 mg)-alone provided information about breast cancer in estrogen-alone users. In the WHI estrogen-alone substudy, after an average follow-up of 7.1 years, daily CE-alone was not associated with an increased risk of invasive breast cancer [relative risk (RR) 0.80]^5 [see Clinical Studies (14.2)].

After a mean follow-up of 5.6 years, the estrogen plus progestin substudy reported an increased risk of invasive breast cancer in women who took daily CE plus MPA. In this substudy, prior use of estrogen-alone or estrogen plus progestin therapy was reported by 26% of the women. The relative risk of invasive breast cancer was 1.24, and the absolute risk was 41 versus 33 cases per 10,000 women-years, for CE plus MPA compared with placebo. Among women who reported prior use of hormone therapy, the relative risk of invasive breast cancer was 1.86, and the absolute risk was 46 versus 25 cases per 10,000 women-years, for CE plus MPA compared with placebo. Among women who reported no prior use of hormone therapy, the relative risk of invasive breast cancer was 1.09, and the absolute risk was 40 versus 36 cases per 10,000 women-years for CE plus MPA compared with placebo. In the same substudy, invasive breast cancers were larger, were more likely to be node positive, and were diagnosed at a more advanced stage in the CE (0.625 mg) plus MPA (2.5 mg) group compared with the placebo group. Metastatic disease was rare, with no apparent difference between the two groups. Other prognostic factors, such as histologic subtype, grade and hormone receptor status did not differ between the groups^6 [see Clinical Studies (14.2)].

Consistent with the WHI clinical trials, observational studies have also reported an increased risk of breast cancer for estrogen plus progestin therapy and a smaller increased risk for estrogen-alone therapy, after several years of use. One large meta-analysis of prospective cohort studies reported increased risks that were dependent upon duration of use and could last up to > 10 years after discontinuation of estrogen plus progestin therapy and estrogen-alone therapy. Extension of the WHI trials also demonstrated increased breast cancer risk associated with estrogen plus progestin therapy.

Observational studies also suggest that the risk of breast cancer was greater, and became apparent earlier, with estrogen plus progestin therapy as compared to estrogen-alone therapy. However, these studies have not found significant variation in the risk of breast cancer among different estrogen plus progestin combinations, doses, or routes of administration.

The use of estrogen-alone and estrogen plus progestin has been reported to result in an increase in abnormal mammograms, requiring further evaluation.

All women should receive yearly breast examinations by a healthcare provider and perform monthly breast self-examinations. In addition, mammography examinations should be scheduled based on patient age, risk factors, and prior mammogram results.

Ovarian Cancer

The WHI estrogen plus progestin substudy reported a statistically non-significant increased risk of ovarian cancer. After an average follow-up of 5.6 years, the relative risk for ovarian cancer for CE plus MPA versus placebo was 1.58 (95% confidence interval [CI], 0.77–3.24). The absolute risk for CE plus MPA versus placebo was 4 versus 3 cases per 10,000 women-years.^7

A meta-analysis of 17 prospective and 35 retrospective epidemiology studies found that women who used hormonal therapy for menopausal symptoms had an increased risk for ovarian cancer. The primary analysis, using case-control comparisons, included 12,110 cancer cases from the 17 prospective studies. The relative risks associated with current use of hormonal therapy was 1.41 (95% CI 1.32 to 1.50); there was no difference in the risk estimates by duration of the exposure (less than 5 years [median of 3 years] vs. greater than 5 years [median of 10 years] of use before the cancer diagnosis). The relative risk associated with combined current and recent use (discontinued use within 5 years before cancer diagnosis) was 1.37 (95% CI 1.27–1.48), and the elevated risk was significant for both estrogen-alone and estrogen plus progestin products. The exact duration of hormone therapy use associated with an increased risk of ovarian cancer, however, is unknown.

5.4 Probable Dementia

In the WHIMS estrogen-alone ancillary study of WHI, a population of 2,947 hysterectomized women 65 to 79 years of age was randomized to daily CE (0.625 mg) -alone or placebo.

After an average follow-up of 5.2 years, 28 women in the estrogen-alone group and 19 women in the placebo group were diagnosed with probable dementia. The relative risk of probable dementia for CE-alone versus placebo was 1.49 (95% CI, 0.83–2.66). The absolute risk of probable dementia for CE-alone versus placebo was 37 versus 25 cases per 10,000 women-years^8 [see Use in Specific Populations (8.5), and Clinical Studies (14.3)].

In the WHIMS estrogen plus progestin ancillary study of WHI, a population of 4,532 postmenopausal women 65 to 79 years of age was randomized to daily CE (0.625 mg) plus MPA (2.5 mg) or placebo.

After an average follow-up of 4 years, 40 women in the CE plus MPA group and 21 women in the placebo group were diagnosed with probable dementia. The relative risk of probable dementia for CE plus MPA versus placebo was 2.05 (95% CI, 1.21–3.48). The absolute risk of probable dementia for CE plus MPA versus placebo was 45 versus 22 cases per 10,000 women-years^8 [see Use in Specific Populations (8.5), and Clinical Studies (14.3)].

When data from the two populations in the WHIMS estrogen-alone and estrogen plus progestin ancillary studies were pooled as planned in the WHIMS protocol, the reported overall relative risk for probable dementia was 1.76 (95% CI, 1.19–2.60). Since both substudies were conducted in women 65 to 79 years of age, it is unknown whether these findings apply to younger postmenopausal women^8 [see Use in Specific Populations (8.5), and Clinical Studies (14.3)].

5.5 Gallbladder Disease

A 2- to 4-fold increase in the risk of gallbladder disease requiring surgery in postmenopausal women receiving estrogens has been reported.

5.6 Hypercalcemia

Estrogen administration may lead to severe hypercalcemia in women with breast cancer and bone metastases. If hypercalcemia occurs, use of the drug should be stopped and appropriate measures taken to reduce the serum calcium level.

5.7 Visual Abnormalities

Retinal vascular thrombosis has been reported in patients receiving estrogens. Discontinue medication pending examination if there is sudden partial or complete loss of vision, or a sudden onset of proptosis, diplopia, or migraine. If examination reveals papilledema or retinal vascular lesions, estrogens should be permanently discontinued.

5.8 Addition of a Progestin When a Woman Has Not Had a Hysterectomy

Studies of the addition of a progestin for 10 or more days of a cycle of estrogen administration, or daily with estrogen in a continuous regimen, have reported a lowered incidence of endometrial hyperplasia than would be induced by estrogen treatment alone. Endometrial hyperplasia may be a precursor to endometrial cancer.

There are, however, possible risks that may be associated with the use of progestins with estrogens compared to estrogen-alone regimens. These include an increased risk of breast cancer.

5.9 Elevated Blood Pressure

In a small number of case reports, substantial increases in blood pressure have been attributed to idiosyncratic reactions to estrogens. In a large, randomized, placebo-controlled clinical trial, a generalized effect of estrogen therapy on blood pressure was not seen.

5.10 Exacerbation of Hypertriglyceridemia

In women with pre-existing hypertriglyceridemia, estrogen therapy may be associated with elevations of plasma triglycerides leading to pancreatitis. Consider discontinuation of treatment if pancreatitis occurs.

5.11 Hepatic Impairment and/or Past History of Cholestatic Jaundice

Estrogens may be poorly metabolized in women with impaired liver function. For women with a history of cholestatic jaundice associated with past estrogen use or with pregnancy, caution should be exercised, and in the case of recurrence, medication should be discontinued.

5.12 Exacerbation of Hypothyroidism

Estrogen administration leads to increased thyroid-binding globulin (TBG) levels. Women with normal thyroid function can compensate for the increased TBG by making more thyroid hormone, thus maintaining free T4 and T3 serum concentrations in the normal range. Women dependent on thyroid hormone replacement therapy who are also receiving estrogens may require increased doses of their thyroid replacement therapy. These women should have their thyroid function monitored in order to maintain their free thyroid hormone levels in an acceptable range.

5.13 Fluid Retention

Estrogens may cause some degree of fluid retention. Women with conditions that might be influenced by this factor, such as a cardiac or renal dysfunction, warrant careful observation when estrogens are prescribed.

5.14 Hypocalcemia

Estrogen therapy should be used with caution in women with hypoparathyroidism as estrogen-induced hypocalcemia may occur.

5.15 Exacerbation of Endometriosis

A few cases of malignant transformation of residual endometrial implants have been reported in women treated post-hysterectomy with estrogen-alone therapy. For women known to have residual endometriosis post-hysterectomy, the addition of progestin should be considered.

5.16 Anaphylactic Reaction and Angioedema

Cases of anaphylaxis, which develop within minutes to hours after taking orally-administered PREMARIN and require emergency management, have been reported in the postmarketing setting. Skin (hives, pruritus, swollen lips-tongue-face) and either respiratory tract (respiratory compromise) or gastrointestinal tract (abdominal pain, vomiting) involvement has been noted.

Angioedema involving the tongue, larynx, face, and feet requiring medical intervention has occurred postmarketing in patients taking orally-administered PREMARIN. If angioedema involves the tongue, glottis, or larynx, airway obstruction may occur. Patients who develop an anaphylactic reaction with or without angioedema after treatment with oral PREMARIN should not receive oral PREMARIN again.

5.17 Hereditary Angioedema

Exogenous estrogens may exacerbate symptoms of angioedema in women with hereditary angioedema.

5.18 Exacerbation of Other Conditions

Estrogen therapy may cause an exacerbation of asthma, diabetes mellitus, epilepsy, migraine, porphyria, systemic lupus erythematosus, and hepatic hemangiomas and should be used with caution in women with these conditions.

5.19 Effects on Barrier Contraception

PREMARIN vaginal cream exposure has been reported to weaken latex condoms. The potential for PREMARIN vaginal cream to weaken and contribute to the failure of condoms, diaphragms, or cervical caps made of latex or rubber should be considered.

5.20 Laboratory Tests

Serum follicle stimulating hormone (FSH) and estradiol levels have not been shown to be useful in the management of moderate to severe symptoms of vulvar and vaginal atrophy.

5.21 Drug-Laboratory Test Interactions

- Accelerated prothrombin time, partial thromboplastin time, and platelet aggregation time; increased platelet count; increased factors II, VII antigen, VIII antigen, VIII coagulant activity, IX, X, XII, VII-X complex, II-VII-X complex, and beta-thromboglobulin; decreased levels of anti-factor Xa and antithrombin III, decreased antithrombin III activity; increased levels of fibrinogen and fibrinogen activity; increased plasminogen antigen and activity.
- Increased thyroid-binding globulin (TBG) leading to increased circulating total thyroid hormone, as measured by protein-bound iodine (PBI), T4 levels (by column or by radioimmunoassay) or T3 levels by radioimmunoassay. T3 resin uptake is decreased, reflecting the elevated TBG. Free T4 and free T3 concentrations are unaltered. Women on thyroid replacement therapy may require higher doses of thyroid hormone.
- Other binding proteins may be elevated in serum, for example, corticosteroid binding globulin (CBG), sex hormone-binding globulin (SHBG), leading to increased total circulating corticosteroids and sex steroids, respectively. Free hormone concentrations, such as testosterone and estradiol, may be decreased. Other plasma proteins may be increased (angiotensinogen/renin substrate, alpha-1-antitrypsin, ceruloplasmin).
- Increased plasma high-density lipoprotein (HDL) and HDL2 cholesterol subfraction, reduced low-density lipoprotein (LDL) cholesterol, increased triglyceride levels.
- Impaired glucose tolerance.

6 ADVERSE REACTIONS

The following serious adverse reactions are discussed elsewhere in the labeling:

- Cardiovascular Disorders [see Boxed Warning, Warnings and Precautions (5.2)]
- Malignant Neoplasms [see Boxed Warning, Warnings and Precautions (5.3)]

6.1 Clinical Trials Experience

Because clinical trials are conducted under widely varying conditions, adverse reaction rates observed in the clinical trial of a drug cannot be directly compared to rates in the clinical trials of another drug and may not reflect the rates observed in practice.

In a 12-week, randomized, double-blind, placebo-controlled trial of PREMARIN vaginal cream (PVC), a total of 423 postmenopausal women received at least 1 dose of study medication and were included in all safety analyses: 143 women in the PVC-21/7 treatment group (0.5 g PVC daily for 21 days, then 7 days off), 72 women in the matching placebo treatment group; 140 women in the PVC-2x/wk treatment group (0.5 g PVC twice weekly), 68 women in the matching placebo treatment group. A 40-week, open-label extension followed, in which a total of 394 women received treatment with PVC, including those subjects randomized at baseline to placebo. In this study, the most common adverse reactions ≥ 1% in the double blind phase are shown below (Table 1) [see Clinical Studies (14.1)].

Table 1: Number (%) of Patients Reporting Treatment Emergent Adverse Reactions ≥ 1% Only
 | Treatment
Body System [Body system totals are not necessarily the sum of individual adverse events, since a patient may report two or more different adverse reactions in the same body system.] /Adverse Reaction | PVC 21/7 N=143 | Placebo 21/7 N=72 | PVC 2×/week N=140 | Placebo 2×/week N=68
 | Number (%) of Patients with Adverse Reaction
Body As A Whole
Abdominal Pain | 1 (0.7) | 1 (1.4) | 0 | 1 (1.5)
Headache | 5 (3.5) | 1 (1.4) | 3 (2.1) | 1 (1.5)
Moniliasis | 2 (1.4) | 1 (1.4) | 1 (0.7) | 0
Pain | 2 (1.4) | 0 | 1 (0.7) | 0
Pelvic Pain | 4 (2.8) | 2 (2.8) | 4 (2.9) | 0
Cardiovascular System
Migraine | 0 | 0 | 0 | 1 (1.5)
Vasodilation | 3 (2.1) | 2 (2.8) | 2 (1.4) | 0
Musculoskeletal System
Muscle Cramp | 2 (1.4) | 0 | 0 | 0
Nervous System
Dizziness | 1 (0.7) | 0 | 0 | 1 (1.5)
Skin and Appendages
Acne | 0 | 0 | 2 (1.4) | 0
Erythema | 0 | 1 (1.4) | 0 | 0
Pruritus | 2 (1.4) | 1 (1.4) | 1 (0.7) | 0
Urogenital System
Breast Enlargement | 1 (0.7) | 1 (1.4) | 0 | 0
Breast Pain | 7 (4.9) | 0 | 3 (2.1) | 0
Dysuria | 2 (1.4) | 0 | 0 | 0
Leukorrhea | 3 (2.1) | 1 (1.4) | 4 (2.9) | 5 (7.4)
Metrorrhagia | 0 | 0 | 0 | 2 (2.9)
Urinary Frequency | 0 | 1 (1.4) | 0 | 0
Urinary Tract Infection | 0 | 1 (1.4) | 0 | 0
Urinary Urgency | 1 (0.7) | 1 (1.4) | 0 | 0
Vaginal Hemorrhage | 2 (1.4) | 0 | 1 (0.7) | 1 (1.5)
Vaginal Moniliasis | 2 (1.4) | 0 | 0 | 0
Vaginitis | 2 (1.4) | 1 (1.4) | 3 (2.1) | 3 (4.4)
Vulvovaginal Disorder | 4 (2.8) | 0 | 3 (2.1) | 2 (2.9)

6.2 Postmarketing Experience

The following adverse reactions have been identified during post-approval use of PREMARIN vaginal cream. Because these reactions are reported voluntarily from a population of uncertain size, it is not always possible to reliably estimate their frequency or establish a causal relationship to drug exposure.

Genitourinary System

Abnormal uterine bleeding or spotting, dysmenorrhea or pelvic pain, increase in size of uterine leiomyomata, vaginitis (including vaginal candidiasis), change in cervical secretion, cystitis-like syndrome, application site reactions of vulvovaginal discomfort, (including burning, irritation, and genital pruritus), endometrial hyperplasia, endometrial cancer, precocious puberty, leukorrhea.

Breasts

Tenderness, enlargement, pain, discharge, fibrocystic breast changes, breast cancer, gynecomastia in males.

Cardiovascular

Deep venous thrombosis, pulmonary embolism, myocardial infarction, stroke, increase in blood pressure.

Gastrointestinal

Nausea, vomiting, abdominal cramps, bloating, increased incidence of gallbladder disease.

Skin

Chloasma that may persist when drug is discontinued, loss of scalp hair, hirsutism, rash.

Eyes

Retinal vascular thrombosis, intolerance to contact lenses.

Central Nervous System

Headache, migraine, dizziness, mental depression, nervousness, mood disturbances, irritability, dementia.

Miscellaneous

Increase or decrease in weight, glucose intolerance, edema, arthralgias, leg cramps, changes in libido, urticaria, exacerbation of asthma, increased triglycerides, hypersensitivity.

Additional postmarketing adverse reactions have been reported in patients receiving other forms of hormone therapy.

7 DRUG INTERACTIONS

No drug interaction studies have been conducted for PREMARIN vaginal cream.

7.1 Metabolic Interactions

In vitro and in vivo studies have shown that estrogens are metabolized partially by cytochrome P450 3A4 (CYP3A4). Therefore, inducers or inhibitors of CYP3A4 may affect estrogen drug metabolism. Inducers of CYP3A4, such as St. John's wort (Hypericum perforatum) preparations, phenobarbital, carbamazepine, and rifampin, may reduce plasma concentrations of estrogens, possibly resulting in a decrease in therapeutic effects and/or changes in the uterine bleeding profile. Inhibitors of CYP3A4, such as erythromycin, clarithromycin, ketoconazole, itraconazole, ritonavir and grapefruit juice, may increase plasma concentrations of estrogens and may result in side effects.

8 USE IN SPECIFIC POPULATIONS

8.1 Pregnancy

Risk Summary

PREMARIN vaginal cream is not indicated for use during pregnancy.

There are no data with the use of PREMARIN vaginal cream in pregnant women; however, epidemiologic studies and meta-analyses have not found an increased risk of genital or nongenital birth defects (including cardiac anomalies and limb-reduction defects) following exposure to combined hormonal contraceptives (estrogen and progestins) before conception or during early pregnancy.

In the U.S. general population, the estimated background risk of major birth defects and miscarriage in clinically recognized pregnancies is 2% to 4% and 15% to 20%, respectively.

8.2 Lactation

Risk Summary

Estrogens are present in human milk and can reduce milk production in breast-feeding women. This reduction can occur at any time but is less likely to occur once breast-feeding is well established.

The developmental and health benefits of breast-feeding should be considered along with the mother’s clinical need for PREMARIN vaginal cream and any potential adverse effects on the breast-fed child from PREMARIN vaginal cream or from the underlying maternal condition.

8.4 Pediatric Use

PREMARIN vaginal cream is not indicated in children. Clinical studies have not been conducted in the pediatric population.

8.5 Geriatric Use

There have not been sufficient numbers of geriatric women involved in clinical studies utilizing PREMARIN vaginal cream to determine whether those over 65 years of age differ from younger subjects in their response to PREMARIN vaginal cream.

The Women's Health Initiative Studies

In the WHI estrogen-alone substudy (daily CE (0.625 mg)-alone versus placebo), there was a higher relative risk of stroke in women greater than 65 years of age [see Warnings and Precautions (5.2), and Clinical Studies (14.2)].

In the WHI estrogen plus progestin substudy (daily CE [0.625 mg] plus MPA [2.5 mg] versus placebo), there was a higher relative risk of nonfatal stroke and invasive breast cancer in women greater than 65 years of age [see Warnings and Precautions (5.2, 5.3), and Clinical Studies (14.2)].

The Women's Health Initiative Memory Study

In the WHIMS ancillary studies of postmenopausal women 65 to 79 years of age, there was an increased risk of developing probable dementia in women receiving estrogen-alone or estrogen plus progestin when compared to placebo [see Warnings and Precautions (5.4), and Clinical Studies (14.3)].

Since both ancillary studies were conducted in women 65 to 79 years of age, it is unknown whether these findings apply to younger postmenopausal women^8 [see Warnings and Precautions (5.4), and Clinical Studies (14.3)].

8.6 Renal Impairment

The effect of renal impairment on the pharmacokinetics of PREMARIN vaginal cream has not been studied.

8.7 Hepatic Impairment

The effect of hepatic impairment on the pharmacokinetics of PREMARIN vaginal cream has not been studied.

10 OVERDOSAGE

Overdosage of estrogen may cause nausea, vomiting, breast tenderness, abdominal pain, drowsiness and fatigue, and withdrawal bleeding may occur in women. Treatment of overdose consists of discontinuation of PREMARIN therapy with institution of appropriate symptomatic care.

11 DESCRIPTION

Each gram of PREMARIN (CE) vaginal cream contains 0.625 mg CE, USP in a nonliquefying base containing cetyl esters wax, cetyl alcohol, white wax, glyceryl monostearate, propylene glycol monostearate, methyl stearate, benzyl alcohol, sodium lauryl sulfate, glycerin, and mineral oil. PREMARIN vaginal cream is applied intravaginally.

PREMARIN vaginal cream contains a mixture of CE obtained exclusively from natural sources, occurring as the sodium salts of water-soluble estrogen sulfates blended to represent the average composition of material derived from pregnant mares' urine. It is a mixture of sodium estrone sulfate and sodium equilin sulfate. It contains as concomitant components, sodium sulfate conjugates, 17 α-dihydroequilin, 17 α-estradiol, and 17 β-dihydroequilin.

12 CLINICAL PHARMACOLOGY

12.1 Mechanism of Action

Endogenous estrogens are largely responsible for the development and maintenance of the female reproductive system and secondary sexual characteristics. Although circulating estrogens exist in a dynamic equilibrium of metabolic interconversions, estradiol is the principal intracellular human estrogen and is substantially more potent than its metabolites, estrone and estriol, at the receptor level.

The primary source of estrogen in normally cycling adult women is the ovarian follicle, which secretes 70 to 500 mcg of estradiol daily, depending on the phase of the menstrual cycle. After menopause, most endogenous estrogen is produced by conversion of androstenedione, which is secreted by the adrenal cortex, to estrone in the peripheral tissues. Thus, estrone and the sulfate-conjugated form, estrone sulfate, are the most abundant circulating estrogens in postmenopausal women.

Estrogens act through binding to nuclear receptors in estrogen-responsive tissues. To date, two estrogen receptors have been identified. These vary in proportion from tissue to tissue.

Circulating estrogens modulate the pituitary secretion of the gonadotropins, luteinizing hormone (LH) and FSH, through a negative feedback mechanism. Estrogens act to reduce the elevated levels of these gonadotropins seen in postmenopausal women.

12.2 Pharmacodynamics

Currently, there are no pharmacodynamic data known for PREMARIN vaginal cream.

12.3 Pharmacokinetics

Absorption

Conjugated estrogens are water soluble and are well-absorbed through the skin, mucous membranes, and the gastrointestinal (GI) tract. The vaginal delivery of estrogens circumvents first-pass metabolism.

A bioavailability study was conducted in 24 postmenopausal women with atrophic vaginitis. The mean (SD) pharmacokinetic parameters for unconjugated estrone, unconjugated estradiol, total estrone, total estradiol and total equilin following 7 once-daily doses of PREMARIN vaginal cream 0.5 g is shown in Table 2.

Table 2: Mean ± SD Pharmacokinetic Parameters of PREMARIN Following Daily Administration (7 Days) of PREMARIN Vaginal Cream 0.5 g in 24 Postmenopausal Women
Pharmacokinetic Profiles of Unconjugated Estrogens
PREMARIN Vaginal Cream 0.5 g
PK Parameters Arithmetic Mean ± SD | Cmax (pg/mL) | Tmax (hr) | AUCss (pg•hr/mL)
Estrone | 42.0 ± 13.9 | 7.4 ± 6.2 | 826 ± 295
Baseline-adjusted estrone | 21.9 ± 13.1 | 7.4 ± 6.2 | 365 ± 255
Estradiol | 12.8 ± 16.6 | 8.5 ± 6.2 | 231 ± 285
Baseline-adjusted estradiol | 9.14 ± 14.7 | 8.5 ± 6.2 | 161 ± 252
Pharmacokinetic Profiles of CE
PREMARIN Vaginal Cream 0.5 g
PK Parameters Arithmetic Mean ± SD | Cmax (ng/mL) | Tmax (hr) | AUCss (ng•hr/mL)
Total estrone | 0.60 ± 0.32 | 6.0 ± 4.0 | 9.75 ± 4.99
Baseline-adjusted total estrone | 0.40 ± 0.28 | 6.0 ± 4.0 | 5.79 ± 3.7
Total estradiol | 0.04 ± 0.04 | 7.7 ± 5.9 | 0.70 ± 0.42
Baseline-adjusted total estradiol | 0.04 ± 0.04 | 7.7 ± 6.0 | 0.49 ± 0.38
Total equilin | 0.12 ± 0.15 | 6.1 ± 4.7 | 3.09 ± 1.37

Distribution

The distribution of exogenous estrogens is similar to that of endogenous estrogens. Estrogens are widely distributed in the body and are generally found in higher concentration in the sex hormone target organs. Estrogens circulate in the blood largely bound to SHBG and albumin.

Metabolism

Exogenous estrogens are metabolized in the same manner as endogenous estrogens. Circulating estrogens exist in a dynamic equilibrium of metabolic interconversions. These transformations take place mainly in the liver. Estradiol is converted reversibly to estrone, and both can be converted to estriol, which is a major urinary metabolite. Estrogens also undergo enterohepatic recirculation via sulfate and glucuronide conjugation in the liver, biliary secretion of conjugates into the intestine, and hydrolysis in the intestine followed by reabsorption. In postmenopausal women, a significant proportion of the circulating estrogens exist as sulfate conjugates, especially estrone sulfate, which serves as a circulating reservoir for the formation of more active estrogens.

Excretion

Estradiol, estrone, and estriol are excreted in the urine along with glucuronide and sulfate conjugates.

Use in Specific Populations

No pharmacokinetic studies were conducted in specific populations, including patients with renal or hepatic impairment.

13 NONCLINICAL TOXICOLOGY

13.1 Carcinogenesis, Mutagenesis, Impairment of Fertility

Long-term continuous administration of natural and synthetic estrogens in certain animal species increases the frequency of carcinomas of the breast, uterus, cervix, vagina, testis, and liver [see Warnings and Precautions (5.3)].

14 CLINICAL STUDIES

14.1 Effects on Vulvar and Vaginal Atrophy

A 12-week, prospective, randomized, double-blind placebo-controlled study was conducted to compare the safety and efficacy of 2 PREMARIN vaginal cream (PVC) regimens 0.5 g (0.3 mg CE) administered twice weekly and 0.5 g (0.3 mg CE) administered sequentially for 21 days on drug followed by 7 days off drug to matching placebo regimens in the treatment of moderate to severe symptoms of vulvar and vaginal atrophy due to menopause. The initial 12-week, double-blind, placebo-controlled phase was followed by an open-label phase to assess endometrial safety through week 52. The study randomized 423 generally healthy postmenopausal women between 44 to 77 years of age (mean 57.8 years), who at baseline had ≤ 5% superficial cells on a vaginal smear, a vaginal pH ≥ 5.0, and who identified a most bothersome moderate to severe symptom of vulvar and vaginal atrophy. The majority (92.2%) of the women were Caucasian (n = 390); 7.8% were Other (n = 33). All subjects were assessed for improvement in the mean change from baseline to Week 12 for the co-primary efficacy variables of: most bothersome symptom of vulvar and vaginal atrophy (defined as the moderate to severe symptom that had been identified by the woman as most bothersome to her at baseline); percentage of vaginal superficial cells and percentage of vaginal parabasal cells; and vaginal pH.

In the 12-week, double-blind phase, a statistically significant mean change between baseline and Week 12 in the symptom of dyspareunia was observed for both of the PREMARIN vaginal cream regimens (0.5 g daily for 21 days, then 7 days off and 0.5 g twice weekly) compared to matching placebo, see Table 3. Also demonstrated for each PREMARIN vaginal cream regimen compared to placebo was a statistically significant increase in the percentage of superficial cells at Week 12 (28%, 21/7 regimen and 26%, twice a week compared to 3% and 1% for matching placebo), a statistically significant decrease in parabasal cells (-61%, 21/7 regimen and -58%, twice a week compared to -21% and -7% for matching placebo) and statistically significant mean reduction between baseline and Week 12 in vaginal pH (-1.62, 21/7 regimen and -1.57, twice a week compared to -0.36 and -0.26 for matching placebo).

Endometrial safety was assessed by endometrial biopsy for all randomly assigned subjects at week 52. For the 155 subjects (83 on the 21/7 regimen, 72 on the twice-weekly regimen) completing the 52-week period with complete follow-up and evaluable endometrial biopsies, there were no reports of endometrial hyperplasia or endometrial carcinoma.

Table 3: Mean Change in Dyspareunia Severity Compared to Placebo MITT Population of Most Bothersome Symptom Score for Dyspareunia, LOCF
Dyspareunia | PVC 0.5 g 21/7 [PVC 21/7 = apply PVC for 21 days and then 7 days of no therapy] | Placebo 0.5 g 21/7 | PVC 0.5 g 2×/wk [PVC 2×/wk = apply PVC twice a week] | Placebo 0.5 g 2×/wk
Baseline | n Mean (SD) 50 2.26 (0.99) | n Mean (SD) 18 2.32 (0.88) | n Mean (SD) 52 2.43 (0.76) | n Mean (SD) 22 2.28 (1.04)
Week 12 | 50 0.77 (1.05) | 18 1.93 (1.03) | 52 0.88 (0.96) | 21 1.63 (1.16)
Change from Baseline at Week 12 | 50 -1.48 (1.17) | 18 -0.40 (1.01) | 52 -1.55 (0.92) | 21 -0.62 (1.23)
P-value vs. Placebo | <0.001 [Comparison of PVC 21/7 with placebo 21/7] | -- | <0.001 [Comparison of PVC 2×/wk with placebo 2×/wk] | --

14.2 Women's Health Initiative Studies

The WHI enrolled approximately 27,000 predominantly healthy postmenopausal women in two substudies to assess the risks and benefits of daily oral CE (0.625 mg)-alone or in combination with MPA (2.5 mg) compared to placebo in the prevention of certain chronic diseases. The primary endpoint was the incidence of CHD (defined as nonfatal MI, silent MI and CHD death), with invasive breast cancer as the primary adverse outcome. A "global index" included the earliest occurrence of CHD, invasive breast cancer, stroke, PE, endometrial cancer (only in the CE plus MPA substudy), colorectal cancer, hip fracture, or death due to other causes. These substudies did not evaluate the effects of CE-alone or CE plus MPA on menopausal symptoms.

WHI Estrogen-Alone Substudy

The WHI estrogen-alone substudy was stopped early because an increased risk of stroke was observed, and it was deemed that no further information would be obtained regarding the risks and benefits of estrogen-alone in predetermined primary endpoints.

Results of the estrogen-alone substudy, which included 10,739 women (average 63 years of age, range 50 to 79; 75.3% White, 15.1% Black, 6.1% Hispanic, 3.6% Other) after an average follow-up of 7.1 years, are presented in Table 4.

Table 4: Relative and Absolute Risk Seen in the Estrogen Alone Substudy of WHI [Adapted from numerous WHI publications. WHI publications can be viewed at www.nhlbi.nih.gov/whi.]
Event | Relative Risk CE vs. Placebo (95% nCI [Nominal confidence intervals unadjusted for multiple looks and multiple comparisons.]) | CE n = 5,310 | Placebo n = 5,429
Event | Relative Risk CE vs. Placebo (95% nCI [Nominal confidence intervals unadjusted for multiple looks and multiple comparisons.]) | Absolute Risk per 10,000 Women-Years
CHD events [Results are based on centrally adjudicated data for an average follow-up of 7.1 years.] | 0.95 (0.78–1.16) | 54 | 57
Non-fatal MI | 0.91 (0.73–1.14) | 40 | 43
CHD death | 1.01 (0.71–1.43) | 16 | 16
All Strokes | 1.33 (1.05–1.68) | 45 | 33
Ischemic stroke | 1.55 (1.19–2.01) | 38 | 25
Deep vein thrombosis, [Not included in "global index."] | 1.47 (1.06–2.06) | 23 | 15
Pulmonary embolism | 1.37 (0.90–2.07) | 14 | 10
Invasive breast cancer | 0.80 (0.62–1.04) | 28 | 34
Colorectal cancer [Results are based on an average follow-up of 6.8 years.] | 1.08 (0.75–1.55) | 17 | 16
Hip fracture | 0.65 (0.45–0.94) | 12 | 19
Vertebral fractures, | 0.64 (0.44–0.93) | 11 | 18
Lower arm/wrist fractures, | 0.58 (0.47–0.72) | 35 | 59
Total fractures, | 0.71 (0.64–0.80) | 144 | 197
Death due to other causes, [All deaths, except from breast or colorectal cancer, definite or probable CHD, PE or cerebrovascular disease.] | 1.08 (0.88–1.32) | 53 | 50
Overall mortality, | 1.04 (0.88–1.22) | 79 | 75
Global Index [A subset of the events was combined in a “global index” defined as the earliest occurrence of CHD events, invasive breast cancer, stroke, pulmonary embolism, colorectal cancer, hip fracture, or death due to other causes.] | 1.02 (0.92–1.13) | 206 | 201

For those outcomes included in the WHI "global index" that reached statistical significance, the absolute excess risk per 10,000 women-years in the group treated with CE-alone was 12 more strokes while the absolute risk reduction per 10,000 women-years was 7 fewer hip fractures.^9 The absolute excess risk of events included in the "global index" was a non-significant 5 events per 10,000 women-years. There was no difference between the groups in terms of all-cause mortality.

No overall difference for primary CHD events (nonfatal MI, silent MI and CHD death) and invasive breast cancer incidence in women receiving CE-alone compared with placebo was reported in final centrally adjudicated results from the estrogen-alone substudy, after an average follow up of 7.1 years. See Table 4.

Centrally adjudicated results for stroke events from the estrogen-alone substudy, after an average follow-up of 7.1 years, reported no significant difference in distribution of stroke subtype or severity, including fatal strokes, in women receiving CE-alone compared to placebo. Estrogen-alone increased the risk for ischemic stroke, and this excess risk was present in all subgroups of women examined.^10

Timing of the initiation of estrogen-alone therapy relative to the start of menopause may affect the overall risk benefit profile. The WHI estrogen-alone substudy stratified by age showed in women 50 to 59 years of age, a non-significant trend toward reduced risk for CHD [hazard ratio (HR) 0.63 (95% CI 0.36–1.09)] and overall mortality [HR 0.71 (95% CI 0.46–1.11)].

WHI Estrogen Plus Progestin Substudy

The WHI estrogen plus progestin substudy was stopped early. According to the predefined stopping rule, after an average follow-up of 5.6 years of treatment, the increased risk of invasive breast cancer and cardiovascular events exceeded the specified benefits included in the "global index." The absolute excess risk of events included in the "global index" was 19 per 10,000 women-years.

For those outcomes included in the WHI "global index" that reached statistical significance after 5.6 years of follow-up, the absolute excess risks per 10,000 women-years in the group treated with CE plus MPA were 7 more CHD events, 8 more strokes, 10 more PEs, and 8 more invasive breast cancers, while the absolute risk reductions per 10,000 women-years were 6 fewer colorectal cancers and 5 fewer hip fractures.

Results of the CE plus MPA substudy, which included 16,608 women (average 63 years of age, range 50 to 79; 83.9% White, 6.8% Black, 5.4% Hispanic, 3.9% Other) are presented in Table 5. These results reflect centrally adjudicated data after an average follow-up of 5.6 years.

Table 5: Relative and Absolute Risk Seen in the Estrogen Plus Progestin Substudy of WHI at an Average of 5.6 Years [Adapted from numerous WHI publications. WHI publications can be viewed at www.nhlbi.nih.gov/whi.] , [Results are based on centrally adjudicated data.]
Event | Relative Risk CE/MPA vs. Placebo (95% nCI [Nominal confidence intervals unadjusted for multiple looks and multiple comparisons.]) | CE/MPA n = 8,506 | Placebo n = 8,102
Event | Relative Risk CE/MPA vs. Placebo (95% nCI [Nominal confidence intervals unadjusted for multiple looks and multiple comparisons.]) | Absolute Risk per 10,000 Women-Years
CHD events | 1.23 (0.99–1.53) | 41 | 34
Non-fatal MI | 1.28 (1.00–1.63) | 31 | 25
CHD death | 1.10 (0.70–1.75) | 8 | 8
All Strokes | 1.31 (1.03–1.68) | 33 | 25
Ischemic stroke | 1.44 (1.09–1.90) | 26 | 18
Deep vein thrombosis [Not included in "global index."] | 1.95 (1.43–2.67) | 26 | 13
Pulmonary embolism | 2.13 (1.45–3.11) | 18 | 8
Invasive breast cancer [Includes metastatic and non-metastatic breast cancer, with the exception of in situ cancer.] | 1.24 (1.01–1.54) | 41 | 33
Colorectal cancer | 0.61 (0.42–0.87) | 10 | 16
Endometrial cancer | 0.81 (0.48–1.36) | 6 | 7
Cervical cancer | 1.44 (0.47–4.42) | 2 | 1
Hip fracture | 0.67 (0.47–0.96) | 11 | 16
Vertebral fractures | 0.65 (0.46–0.92) | 11 | 17
Lower arm/wrist fractures | 0.71 (0.59–0.85) | 44 | 62
Total fractures | 0.76 (0.69–0.83) | 152 | 199
Overall Mortality [All deaths, except from breast or colorectal cancer, definite or probable CHD, PE or cerebrovascular disease.] | 1.00 (0.83–1.19) | 52 | 52
Global Index [A subset of the events was combined in a "global index" defined as the earliest occurrence of CHD events, invasive breast cancer, stroke, pulmonary embolism, colorectal cancer, hip fracture, or death due to other causes.] | 1.13 (1.02–1.25) | 184 | 165

Timing of the initiation of estrogen plus progestin therapy relative to the start of menopause may affect the overall risk benefit profile. The WHI estrogen plus progestin substudy stratified by age showed in women 50 to 59 years of age, a non-significant trend toward reduced risk for overall mortality [HR 0.69 (95% CI, 0.44–1.07)].

14.3 Women's Health Initiative Memory Study

The WHIMS estrogen-alone ancillary study of WHI enrolled 2,947 predominantly healthy hysterectomized postmenopausal women 65 to 79 years of age and older (45% were 65 to 69 years of age; 36% were 70 to 74 years of age; 19% were 75 years of age and older) to evaluate the effects of daily CE (0.625 mg)-alone on the incidence of probable dementia (primary outcome) compared to placebo.

After an average follow-up of 5.2 years, the relative risk of probable dementia for CE-alone versus placebo was 1.49 (95% CI, 0.83–2.66). The absolute risk of probable dementia for CE-alone versus placebo was 37 versus 25 cases per 10,000 women-years. Probable dementia as defined in this study included Alzheimer's disease (AD), vascular dementia (VaD) and mixed types (having features of both AD and VaD). The most common classification of probable dementia in the treatment group and the placebo group was AD. Since the ancillary study was conducted in women 65 to 79 years of age, it is unknown whether these findings apply to younger postmenopausal women [see Warnings and Precautions (5.4), and Use in Specific Populations (8.5)].

The WHIMS estrogen plus progestin ancillary study of WHI enrolled 4,532 predominantly healthy postmenopausal women 65 years of age and older (47% were 65 to 69 years of age; 35% were 70 to 74 years; 18% were 75 years of age and older) to evaluate the effects of daily CE (0.625 mg) plus MPA (2.5 mg) on the incidence of probable dementia (primary outcome) compared to placebo.

After an average follow-up of 4 years, the relative risk of probable dementia for CE plus MPA versus placebo was 2.05 (95% CI, 1.21–3.48). The absolute risk of probable dementia for CE plus MPA versus placebo was 45 versus 22 per 10,000 women-years. Probable dementia as defined in this study included AD, VaD and mixed types (having features of both AD and VaD). The most common classification of probable dementia in the treatment group and the placebo group was AD. Since the ancillary study was conducted in women 65 to 79 years of age, it is unknown whether these findings apply to younger postmenopausal women [see Warnings and Precautions (5.4), and Use in Specific Populations (8.5)].

When data from the two populations were pooled as planned in the WHIMS protocol, the reported overall relative risk for probable dementia was 1.76 (95% CI, 1.19–2.60). Differences between groups became apparent in the first year of treatment. It is unknown whether these findings apply to younger postmenopausal women [see Warnings and Precautions (5.4), and Use in Specific Populations (8.5)].

15 REFERENCES

1. Rossouw JE, et al. Postmenopausal Hormone Therapy and Risk of Cardiovascular Disease by Age and Years Since Menopause. JAMA. 2007;297:1465–1477.
2. Hsia J, et al. Conjugated Equine Estrogens and Coronary Heart Disease. Arch Int Med. 2006;166:357–365.
3. Curb JD, et al. Venous Thrombosis and Conjugated Equine Estrogen in Women Without a Uterus. Arch Int Med. 2006;166:772–780.
4. Cushman M, et al. Estrogen Plus Progestin and Risk of Venous Thrombosis. JAMA. 2004;292:1573–1580.
5. Stefanick ML, et al. Effects of Conjugated Equine Estrogens on Breast Cancer and Mammography Screening in Postmenopausal Women With Hysterectomy. JAMA. 2006;295:1647–1657.
6. Chlebowski RT, et al. Influence of Estrogen Plus Progestin on Breast Cancer and Mammography in Healthy Postmenopausal Women. JAMA. 2003;289:3234–3253.
7. Anderson GL, et al. Effects of Estrogen Plus Progestin on Gynecologic Cancers and Associated Diagnostic Procedures. JAMA. 2003;290:1739–1748.
8. Shumaker SA, et al. Conjugated Equine Estrogens and Incidence of Probable Dementia and Mild Cognitive Impairment in Postmenopausal Women. JAMA. 2004;291:2947–2958.
9. Jackson RD, et al. Effects of Conjugated Equine Estrogen on Risk of Fractures and BMD in Postmenopausal Women With Hysterectomy: Results From the Women's Health Initiative Randomized Trial. J Bone Miner Res. 2006;21:817–828.
10. Hendrix SL, et al. Effects of Conjugated Equine Estrogen on Stroke in the Women's Health Initiative. Circulation. 2006;113:2425–2434.

16 HOW SUPPLIED/STORAGE AND HANDLING

16.1 How Supplied

PREMARIN vaginal cream—Each gram contains 0.625 mg conjugated estrogens, USP.

Combination package: Each contains a net wt. of 1.06 oz (30 g) tube with plastic applicator(s) calibrated in 0.5 g increments to a maximum of 2 g (NDC 0046-0872-21).

16.2 Storage and Handling

Store at 20° to 25°C (68° to 77°F); excursions permitted to 15° to 30°C (59° to 86°F) [see USP Controlled Room Temperature].

17 PATIENT COUNSELING INFORMATION

Advise the patient to read the FDA-approved patient labeling (Patient Information).

17.1 Vaginal Bleeding

Inform postmenopausal women of the importance of reporting vaginal bleeding to their healthcare provider as soon as possible [see Warnings and Precautions (5.3)].

17.2 Possible Serious Adverse Reactions with Estrogens

Inform postmenopausal women of possible serious adverse reactions of estrogen-alone therapy including Cardiovascular Disorders, Malignant Neoplasms, and Probable Dementia [see Warnings and Precautions (5.2, 5.3, 5.4)].

17.3 Possible Less Serious but Common Adverse Reactions with Estrogens

Inform postmenopausal women of possible less serious but common adverse reactions of estrogen-alone therapy such as headache, breast pain and tenderness, nausea and vomiting.

This product’s labeling may have been updated. For the most recent prescribing information, please visit www.pfizer.com.

LAB-0498-9.0

PATIENT INFORMATION
PREMARIN® (prem-uh-rin)
(Conjugated estrogens) vaginal cream

Read this PATIENT INFORMATION before you start using PREMARIN vaginal cream and read what you get each time you refill your PREMARIN vaginal cream prescription. There may be new information. This information does not take the place of talking to your healthcare provider about your menopausal symptoms or your treatment.

What is the most important information I should know about PREMARIN vaginal cream (an estrogen mixture)?

- Using estrogen-alone may increase your chance of getting cancer of the uterus (womb)
  Report any unusual vaginal bleeding right away while you are using PREMARIN vaginal cream. Vaginal bleeding after menopause may be a warning sign of cancer of the uterus (womb). Your healthcare provider should check any unusual vaginal bleeding to find out the cause.
- Do not use estrogen-alone to prevent heart disease, heart attacks, strokes or dementia (decline in brain function)
- Using estrogen-alone may increase your chances of getting strokes or blood clots
- Using estrogen-alone may increase your chance of getting dementia, based on a study of women of 65 years of age or older
- Do not use estrogens with progestins to prevent heart disease, heart attacks, strokes, or dementia
- Using estrogens with progestins may increase your chances of getting heart attacks, strokes, breast cancer, or blood clots
- Using estrogens with progestins may increase your chance of getting dementia, based on a study of women age 65 years of age or older
- You and your healthcare provider should talk regularly about whether you still need treatment with PREMARIN vaginal cream

What is PREMARIN vaginal cream?

PREMARIN vaginal cream is a medicine that contains a mixture of estrogen hormones.

What is PREMARIN vaginal cream used for?

PREMARIN vaginal cream is used after menopause to:

- Treat menopausal changes in and around the vagina
  You and your healthcare provider should talk regularly about whether you still need treatment with PREMARIN vaginal cream to control these problems.
- Treat painful intercourse caused by menopausal changes of the vagina

Who should not use PREMARIN vaginal cream?

Do not start using PREMARIN vaginal cream if you:

- Have unusual vaginal bleeding
- Currently have or have had certain cancers
  Estrogens may increase the chance of getting certain types of cancers, including cancer of the breast or uterus. If you have or have had cancer, talk with your healthcare provider about whether you should use PREMARIN vaginal cream.
- Had a stroke or heart attack
- Currently have or have had blood clots
- Currently have or have had liver problems
- Have been diagnosed with a bleeding disorder
- Are allergic to PREMARIN vaginal cream or any of its ingredients
  See the end of this leaflet for a list of ingredients in PREMARIN vaginal cream.

Tell your healthcare provider:

- If you have unusual vaginal bleeding
  Vaginal bleeding after menopause may be a warning sign of cancer of the uterus (womb). Your healthcare provider should check any unusual vaginal bleeding to find out the cause.
- About all of your medical problems
  Your healthcare provider may need to check you more carefully if you have certain conditions, such as asthma (wheezing), epilepsy (seizures), diabetes, migraine, endometriosis, lupus, problems with your heart, liver, thyroid, kidneys, or have high calcium levels in your blood.
- About all the medicines you take
  This includes prescription and nonprescription medicines, vitamins, and herbal supplements. Some medicines may affect how PREMARIN vaginal cream works. PREMARIN vaginal cream may also affect how your other medicines work.
- If you are going to have surgery or will be on bedrest
  You may need to stop using PREMARIN vaginal cream.
- If you are pregnant or think you may be pregnant
  PREMARIN vaginal cream is not for pregnant women
- If you are breast feeding
  The hormones in PREMARIN vaginal cream can pass into your breast milk.

How should I use PREMARIN vaginal cream?

PREMARIN vaginal cream is a cream that you place in your vagina with the applicator provided with the cream.

- Take the dose recommended by your healthcare provider and talk to him or her about how well that dose is working for you
- Estrogens should be used at the lowest dose possible for your treatment only as long as needed. You and your healthcare provider should talk regularly (for example, every 3 to 6 months) about the dose you are using and whether you still need treatment with PREMARIN vaginal cream
- Step 1. Remove cap from tube.
- Step 2. Screw nozzle end of applicator onto tube (Figure A).

Figure A

Step 3. Gently squeeze tube from the bottom to force sufficient cream into the barrel to provide the prescribed dose. Use the marked stopping points on the applicator to measure the correct dose, as prescribed by your healthcare provider (Figure B).

Figure B

Step 4. Unscrew applicator from tube.
Step 5. Lie on back with knees drawn up. To deliver medication, gently insert applicator deeply into vagina and press plunger downward to its original position (Figure C).

Figure C

Step 6. TO CLEANSE: Pull plunger to remove it from barrel. Wash with mild soap and warm water (Figure D).
DO NOT BOIL OR USE HOT WATER.

Figure D

What are the possible side effects of PREMARIN vaginal cream?

PREMARIN vaginal cream is only used in and around the vagina; however, the risks associated with oral estrogens should be taken into account.

Side effects are grouped by how serious they are and how often they happen when you are treated.

Serious, but less common side effects include:

- Heart attack
- Stroke
- Blood clots
- Breast cancer
- Cancer of the lining of the uterus (womb)
- Cancer of the ovary
- Dementia
- High or low blood calcium
- Gallbladder disease
- Visual abnormalities
- High blood pressure
- High levels of fat (triglycerides) in your blood
- Liver problems
- Changes in your thyroid hormone levels
- Fluid retention
- Cancer changes of endometriosis
- Enlargement of benign tumors of the uterus ("fibroids")
- Severe allergic reactions
- Changes in certain laboratory test results, such as high blood sugar

Call your healthcare provider right away if you get any of the following warning signs or any other unusual symptoms that concern you:

- New breast lumps
- Unusual vaginal bleeding
- Changes in vision or speech
- Sudden new severe headaches
- Severe pains in your chest or legs with or without shortness of breath, weakness and fatigue
- Swelling of the face, lips, and tongue with or without red itchy bumps

Common side effects of PREMARIN include:

- Headache
- Breast pain
- Irregular vaginal bleeding or spotting
- Stomach or abdominal cramps, bloating
- Nausea and vomiting
- Hair loss
- Fluid retention
- Vaginal yeast infection
- Reactions from inserting PREMARIN vaginal cream, such as vaginal burning, irritation, and itching

These are not all the possible side effects of PREMARIN vaginal cream. For more information, ask your healthcare provider or pharmacist for advice about side effects. You may report side effects to FDA at 1-800-FDA-1088.

What can I do to lower my chances of getting a serious side effect with PREMARIN vaginal cream?

- Talk with your healthcare provider regularly about whether you should continue using PREMARIN vaginal cream
- If you have a uterus, talk to your healthcare provider about whether the addition of a progestin is right for you
  The addition of a progestin is generally recommended for women with a uterus to reduce the chance of getting cancer of the uterus. See your healthcare provider right away if you get vaginal bleeding while using PREMARIN vaginal cream
- Have a pelvic exam, breast exam and mammogram (breast X-ray) every year unless your healthcare provider tells you something else
  If members of your family have had breast cancer or if you have ever had breast lumps or an abnormal mammogram, you may need to have breast exams more often
- If you have high blood pressure, high cholesterol (fat in the blood), diabetes, are overweight, or if you use tobacco, you may have higher chances for getting heart disease
  Ask your healthcare provider for ways to lower your chances of getting heart disease.

General information about the safe and effective use of PREMARIN vaginal cream

Medicines are sometimes prescribed for conditions that are not mentioned in patient information leaflets. Do not use PREMARIN vaginal cream for conditions for which it was not prescribed. Do not give PREMARIN vaginal cream to other people, even if they have the same symptoms you have. It may harm them.

Keep PREMARIN vaginal cream out of the reach of children.

Latex or rubber condoms, diaphragms and cervical caps may be weakened and fail when they come into contact with PREMARIN vaginal cream.

This leaflet provides a summary of the most important information about PREMARIN vaginal cream. If you would like more information, talk with your healthcare provider or pharmacist. You can ask for information about PREMARIN vaginal cream that is written for health professionals.

What are the ingredients in PREMARIN vaginal cream?

PREMARIN vaginal cream contains a mixture of conjugated estrogens, which are a mixture of sodium estrone sulfate and sodium equilin sulfate and other components, including sodium sulfate conjugates: 17 α-dihydroequilin, 17 α-estradiol, and 17 β-dihydroequilin. PREMARIN vaginal cream also contains cetyl esters wax, cetyl alcohol, white wax, glyceryl monostearate, propylene glycol monostearate, methyl stearate, benzyl alcohol, sodium lauryl sulfate, glycerin, and mineral oil.

PREMARIN vaginal cream—Each gram contains 0.625 mg conjugated estrogens, USP.

Combination package: Each contains a net wt. of 1.06 oz (30 g) tube with plastic applicator(s) calibrated in 0.5 g increments to a maximum of 2 g (NDC 0046-0872-21).

Store at 20° to 25°C (68° to 77°F); excursions permitted to 15° to 30°C (59° to 86°F) [see USP Controlled Room Temperature].

This product's labeling may have been updated. For the most recent prescribing information, please visit www.pfizer.com.

LAB-0519-8.0
Revised 04/2025

PRINCIPAL DISPLAY PANEL - 30 g Tube Label

NDC 0046-0872-21

Premarin®
(conjugated estrogens)
vaginal cream

0.625
mg/g

Rx only

Net Wt. 1.06 oz.
(30 g)

PRINCIPAL DISPLAY PANEL - 30 g Tube Carton

NDC 0046-0872-21

Premarin®
(conjugated estrogens)
vaginal cream

0.625
mg/g

Rx only

Pfizer

Net Wt. 1.06 oz.
(30 g)

This product also contains
cetyl esters wax, cetyl
alcohol, white wax, glyceryl
monostearate, propylene
glycol monostearate, methyl
stearate, benzyl alcohol,
sodium lauryl sulfate,
glycerin, and mineral oil.

2 Applicators enclosed

For vaginal use only.

Usual Dosage: See
accompanying information.